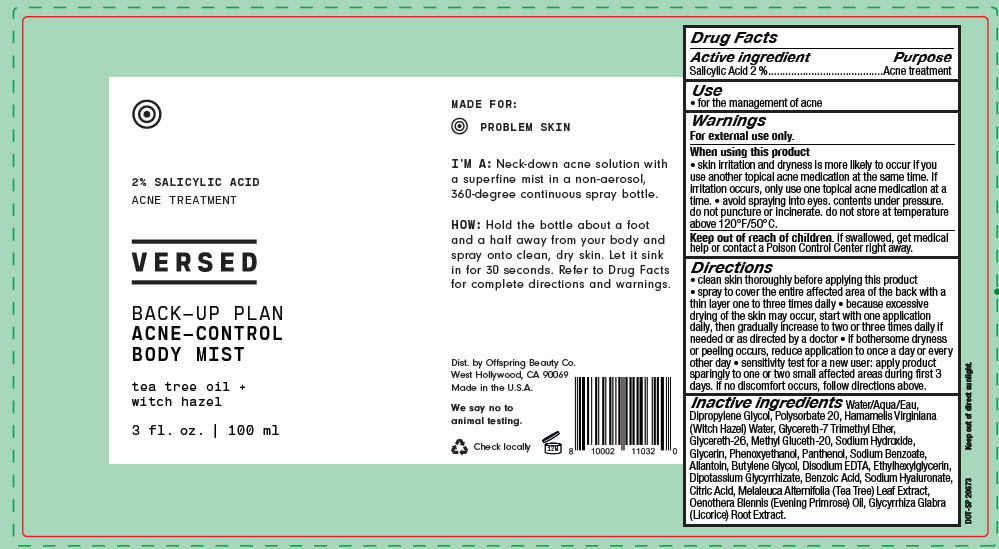 DRUG LABEL: BACK-UP PLAN ACNE-CONTROL BODY MIST
NDC: 73690-023 | Form: SPRAY
Manufacturer: Offspring Beauty Co.
Category: otc | Type: HUMAN OTC DRUG LABEL
Date: 20240104

ACTIVE INGREDIENTS: Salicylic Acid 20 mg/1 mL
INACTIVE INGREDIENTS: WATER; DIPROPYLENE GLYCOL; POLYSORBATE 20; HAMAMELIS VIRGINIANA TOP WATER; GLYCERETH-7 TRIMETHYL ETHER; GLYCERETH-26; METHYL GLUCETH-20; SODIUM HYDROXIDE; GLYCERIN; PHENOXYETHANOL; PANTHENOL; SODIUM BENZOATE; ALLANTOIN; BUTYLENE GLYCOL; EDETATE DISODIUM ANHYDROUS; ETHYLHEXYLGLYCERIN; GLYCYRRHIZINATE DIPOTASSIUM; HYALURONATE SODIUM; MELALEUCA ALTERNIFOLIA LEAF; EVENING PRIMROSE OIL; CITRIC ACID MONOHYDRATE; GLYCYRRHIZA GLABRA; BENZOIC ACID

BACK-UP PLAN ACNE-CONTROL BODY MIST

Drug Facts

Active ingredient

Salicylic Acid 2 %

Purpose

Acne treatment

Use

- for the management of acne

Warnings

For external use only.

When using this product

- skin irritation and dryness is more likely to occur if you use another topical acne medication at the same time. If irritation occurs, only use one topical acne medication at a time.
- avoid spraying into eyes. contents under pressure. do not puncture or incinerate. do not store at temperature above 120°F/50°C.

Keep out of reach of children. if swallowed, get medical help or contact a Poison Control Center right away.

Directions

- clean skin thoroughly before applying this product
- spray to cover the entire affected area of the back with a thin layer one to three times daily
- because excessive drying of the skin may occur, start with one application daily, then gradually increase to two or three times daily if needed or as directed by a doctor
- if bothersome dryness or peeling occurs, reduce application to once a day or every other day
- sensitivity test for a new user: apply product sparingly to one or two small affected areas during first 3 days. if no discomfort occurs, follow directions above.

Inactive ingredients

Water/Aqua/Eau, Dipropylene Glycol, Polysorbate 20, Hamamelis Virginiana (Witch Hazel) Water, Glycereth-7 Trimethyl Ether, Glycereth-26, Methyl Gluceth-20, Sodium Hydroxide, Glycerin, Phenoxyethanol, Panthenol, Sodium Benzoate, Allantoin, Butylene Glycol, Disodium EDTA, Ethylhexylglycerin, Dipotassium Glycyrrhizate, Benzoic Acid, Sodium Hyaluronate, Citric Acid, Melaleuca Alternifolia (Tea Tree) Leaf Extract, Oenothera Biennis (Evening Primrose) Oil, Glycyrrhiza Glabra (Licorice) Root Extract.

Dist. by Offspring Beauty Co.
West Hollywood, CA 90069

PRINCIPAL DISPLAY PANEL - 100 ml Bottle Label

2% SALICYLIC ACID
ACNE TREATMENT

VERSED

BACK-UP PLAN
ACNE-CONTROL
BODY MIST

tea tree oil +
witch hazel

3 fl. oz. | 100 ml